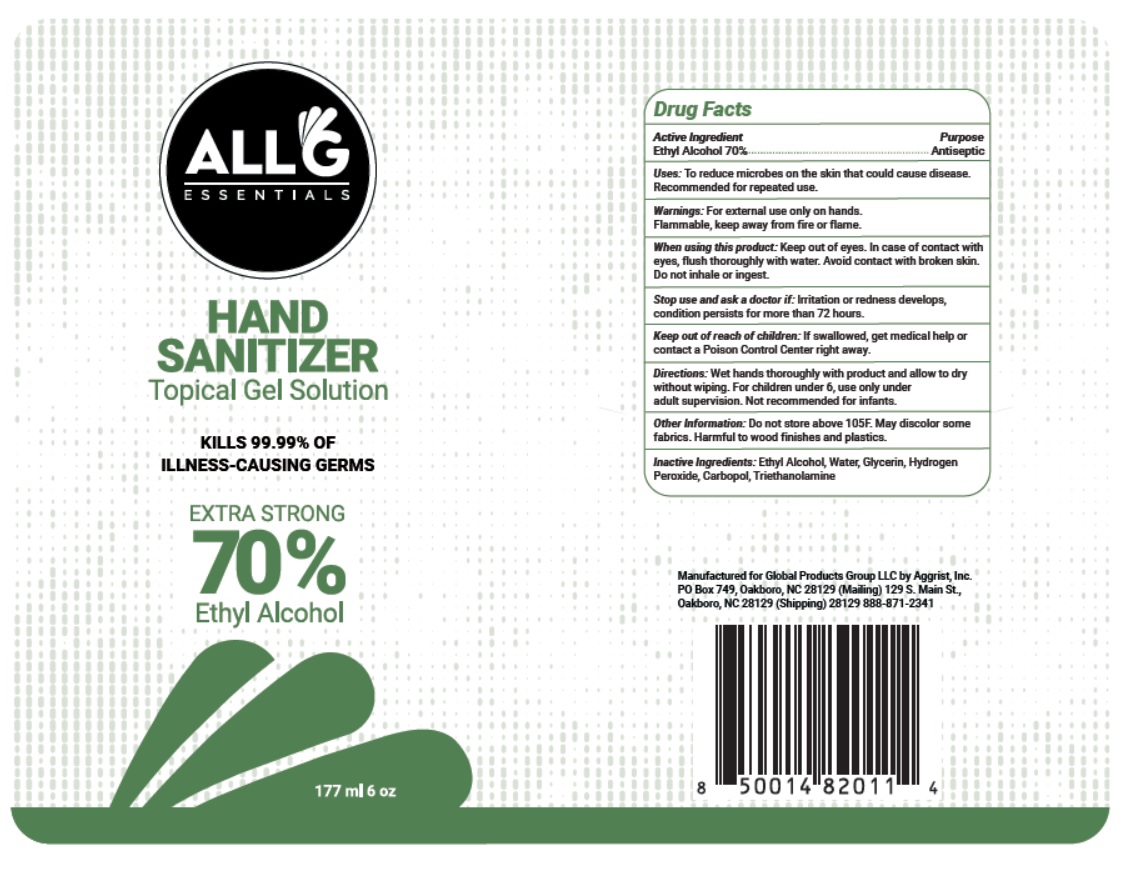 DRUG LABEL: All G ESSENTIALS HAND SANITIZER
NDC: 78285-175 | Form: GEL
Manufacturer: AGGRIST INC
Category: otc | Type: HUMAN OTC DRUG LABEL
Date: 20200604

ACTIVE INGREDIENTS: ALCOHOL 70 mL/100 mL
INACTIVE INGREDIENTS: WATER; GLYCERIN; HYDROGEN PEROXIDE; CARBOMER HOMOPOLYMER, UNSPECIFIED TYPE; TROLAMINE

All G ESSENTIALS HAND SANITIZER

Active Ingredient

Ethyl Alcohol 70%

Purpose

Antiseptic

INDICATIONS AND USAGE

Uses: To reduce microbes on the skin that could cause disease. Recommended for repeated use.

Warnings: For external use only on hands.
Flammable, keep away from fire or flame.
When using this product: Keep out of eyes. In case of contact with eyes, flush thoroughly with water. Avoid contact with broken skin. Do not inhale or ingest.
Stop use and ask a doctor if: Irritation or redness develops, condition persists for more than 72 hours.

Keep out of reach of children: If swallowed, get medical help or contact a Poison Control Center right away.

DOSAGE AND ADMINISTRATION

Directions: Wet hands thoroughly with product and allow to dry without wiping. For children under 6, use only under adult supervision. Not recommended for infants.

Other Information: Do not store above 105F. May discolor some fabrics. Harmful to wood finishes and plastics.

INACTIVE INGREDIENT

Inactive Ingredients: Ethyl Alcohol, Water, Glycerin, Hydrogen Peroxide, Carbopol, Triethanolamine

KILLS 99.99% OF ILLNESS-CAUSING GERMS

EXTRA STRONG 70% Ethyl Alcohol

Manufactured for Global Products Group LLC by Aggrist, Inc.
PO Box 749, Oakboro, NC 28129 (Mailing) 129 S. Main St.,
Oakboro, NC 28129 (Shipping) 28129 888-871-2341